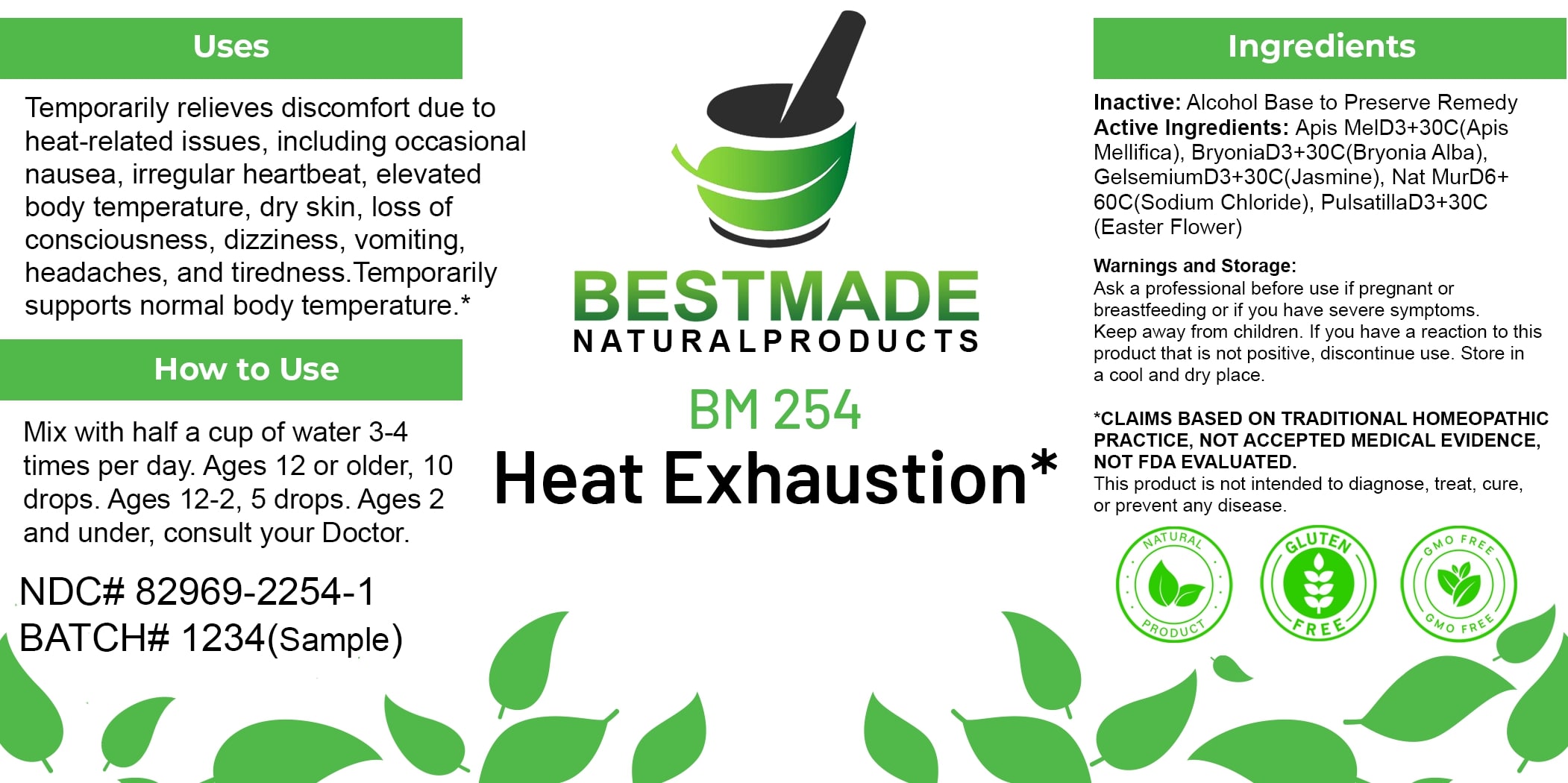 DRUG LABEL: Bestmade Natural Products BM254
NDC: 82969-2254 | Form: LIQUID
Manufacturer: Bestmade Natural Products
Category: homeopathic | Type: HUMAN OTC DRUG LABEL
Date: 20250306

ACTIVE INGREDIENTS: BRYONIA ALBA ROOT 30 [hp_C]/30 [hp_C]; PULSATILLA PRATENSIS 30 [hp_C]/30 [hp_C]; SODIUM CHLORIDE 30 [hp_C]/30 [hp_C]; GELSEMIUM SEMPERVIRENS ROOT 30 [hp_C]/30 [hp_C]; APIS MELLIFERA 30 [hp_C]/30 [hp_C]
INACTIVE INGREDIENTS: ALCOHOL 30 [hp_C]/30 [hp_C]

BM254

DOSAGE AND ADMINISTRATION

How to Use

Mix with half a cup of water 3-4 times per day. Ages 12 or older, 10 drops. Ages 12-2, 5 drops. Ages 2 and under, consult your Doctor.

INACTIVE INGREDIENT

Ingredients

Inactive: Alcohol Base to Preserve Remedy

ACTIVE INGREDIENT

Active Ingredients: Apis Mel D3+30C (Apis Mellifica), Bryonia D3+30C (Bryonia Alba), Gelsemium D3+30C (Jasmine), Nat Mur D6+60C (Sodium Chloride), Pulsatilla D3+30C (Easter Flower)

Uses

Temporarily relieves discomfort due to heat-related issues, including occasional nausea, irregular heartbeat, elevated body temperature, dry skin, loss of consciousness, dizziness, vomiting, headaches, and tiredness. Temporarily supports normal body temperature.*

*CLAIMS BASED ON TRADITIONAL HOMEOPATHIC PRACTICE, NOT ACCEPTED MEDICAL EVIDENCE, NOT FDA EVALUATED.

This product is not intended to diagnose, treat, cure, or prevent any disease.

Uses

Temporarily relieves discomfort due to heat-related issues, including occasional nausea, irregular heartbeat, elevated body temperature, dry skin, loss of consciousness, dizziness, vomiting, headaches, and tiredness. Temporarily supports normal body temperature.*

*CLAIMS BASED ON TRADITIONAL HOMEOPATHIC PRACTICE, NOT ACCEPTED MEDICAL EVIDENCE, NOT FDA EVALUATED.

This product is not intended to diagnose, treat, cure, or prevent any disease.

KEEP OUT OF REACH OF CHILDREN

Warnings and Storage:

Ask a professional before use if pregnant or breastfeeding or if you have severe symptoms. Keep away from children. If you have a reaction to this product that is not positive, discontinue use. Store in a cool and dry place.

Warnings and Storage:

Ask a professional before use if pregnant or breastfeeding or if you have severe symptoms. Keep away from children. If you have a reaction to this product that is not positive, discontinue use. Store in a cool and dry place.

*CLAIMS BASED ON TRADITIONAL HOMEOPATHIC PRACTICE, NOT ACCEPTED MEDICAL EVIDENCE, NOT FDA EVALUATED.

This product is not intended to diagnose, treat, cure, or prevent any disease.

Entire package label